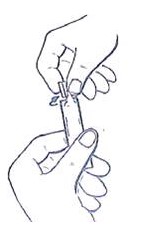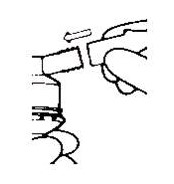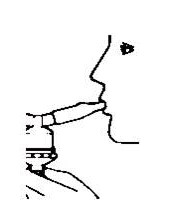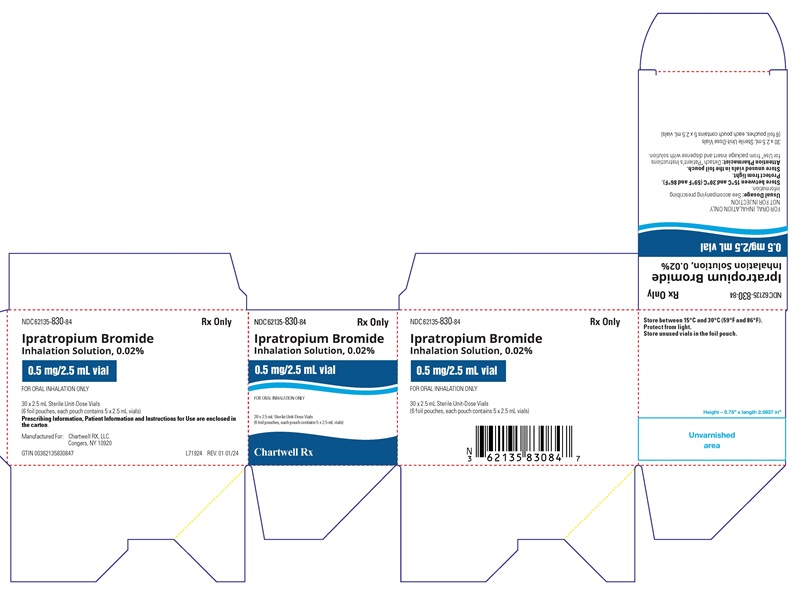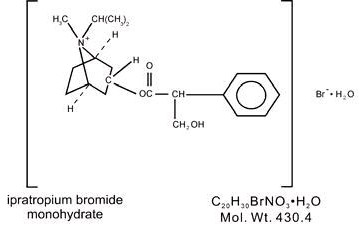 DRUG LABEL: Ipratropium Bromide
NDC: 62135-830 | Form: SOLUTION
Manufacturer: Chartwell RX, LLC
Category: prescription | Type: HUMAN PRESCRIPTION DRUG LABEL
Date: 20251202

ACTIVE INGREDIENTS: IPRATROPIUM BROMIDE 0.5 mg/2.5 mL
INACTIVE INGREDIENTS: WATER; SODIUM CHLORIDE; HYDROCHLORIC ACID

Ipratropium Bromide Inhalation Solution, 0.02%
FOR INHALATION USE ONLY – NOT FOR INJECTION

DESCRIPTION

The active ingredient in ipratropium bromide inhalation solution is ipratropium bromide monohydrate. It is an anticholinergic bronchodilator chemically described as 8-Azoniabicyclo [3.2.1]-octane,-3-(3-hydroxy-1-oxo-2-phenylpropoxy)-8-methyl-8-(1-methylethyl)-, bromide, monohydrate (endo, syn)-,(±)-; a synthetic quaternary ammonium compound, chemically related to atropine.

Ipratropium bromide is a white crystalline substance, freely soluble in water and lower alcohols. It is a quaternary ammonium compound and thus exists in an ionized state in aqueous solutions. It is relatively insoluble in non-polar media.

Ipratropium bromide inhalation solution is administered by oral inhalation with the aid of a nebulizer. Each mL contains ipratropium bromide 0.02% (anhydrous basis) in a sterile, preservative-free, isotonic saline solution, pH-adjusted to 3.4 (3 to 4) with hydrochloric acid.

CLINICAL PHARMACOLOGY

Ipratropium bromide is an anticholinergic (parasympatholytic) agent that, based on animal studies, appears to inhibit vagally-mediated reflexes by antagonizing the action of acetylcholine, the transmitter agent released from the vagus nerve. Anticholinergics prevent the increases in intracellular concentration of cyclic guanosine monophosphate (cyclic GMP) that are caused by interaction of acetylcholine with the muscarinic receptor on bronchial smooth muscle.

The bronchodilation following inhalation of ipratropium bromide inhalation solution is primarily a local, site-specific effect, not a systemic one. Much of an administered dose is swallowed but not absorbed, as shown by fecal excretion studies. Following nebulization of a 2 mg dose, a mean 7% of the dose was absorbed into the systemic circulation either from the surface of the lung or from the gastrointestinal tract. The half-life of elimination is about 1.6 hours after intravenous administration. Ipratropium bromide is minimally (0 to 9% in vitro) bound to plasma albumin and a 1-acid glycoproteins. It is partially metabolized. Autoradiographic studies in rats have shown that ipratropium bromide does not penetrate the blood-brain barrier. Ipratropium bromide inhalation solution has not been studied in patients with hepatic or renal insufficiency. It should be used with caution in those patient populations.

In controlled twelve-week studies in patients with bronchospasm associated with chronic obstructive pulmonary disease (chronic bronchitis and emphysema) significant improvements in pulmonary function (FEV1increases of 15% or more) occurred within 15 to 30 minutes, reached a peak in 1-2 hours, and persisted for periods of 4-5 hours in the majority of patients, with about 25-38% of the patients demonstrating increases of 15% or more for at least 7-8 hours. Continued effectiveness of ipratropium bromide was demonstrated throughout the 12-week period. In addition, significant increases in forced vital capacity (FVC) have been demonstrated. However, ipratropium bromide did not consistently produce significant improvement in subjective symptom scores nor in quality of life scores over the 12-week duration of study. Additional controlled 12-week studies were conducted to evaluate the safety and effectiveness of ipratropium bromide inhalation solution administered concomitantly with the beta adrenergic bronchodilator solutions metaproterenol and albuterol compared with the administration of each of the beta agonists alone. Combined therapy produced significant additional improvement in FEV1and FVC. On combined therapy, the median duration of 15% improvement in FEV1was 5-7 hours, compared with 3-4 hours in patients receiving a beta agonist alone.

INDICATIONS AND USAGE

Ipratropium bromide inhalation solution administered either alone or with other bronchodilators, especially beta adrenergics, is indicated as a bronchodilator for maintenance treatment of bronchospasm associated with chronic obstructive pulmonary disease, including chronic bronchitis and emphysema.

CONTRAINDICATIONS

Ipratropium bromide is contraindicated in known or suspected cases of hypersensitivity to ipratropium bromide, or to atropine and its derivatives.

WARNINGS

The use of ipratropium bromide inhalation solution as a single agent for the relief of bronchospasm in acute COPD exacerbation has not been adequately studied. Drugs with faster onset of action may be preferable as initial therapy in this situation. Combination of ipratropium bromide inhalation solution and beta agonists has not been shown to be more effective than either drug alone in reversing the bronchospasm associated with acute COPD exacerbation.

Immediate hypersensitivity reactions may occur after administration of ipratropium bromide, as demonstrated by rare cases of urticaria, angioedema, rash, bronchospasm and oropharyngeal edema.

PRECAUTIONS

General

Ipratropium bromide should be used with caution in patients with narrow angle glaucoma, prostatic hypertrophy or bladder neck obstruction.

Information for Patients

Patients should be advised that mydriasis, temporary blurring of vision, precipitation or worsening of narrow-angle glaucoma or eye pain may result if the solution comes into direct contact with the eyes. Use of a nebulizer with a mouthpiece rather than a face mask may be preferable, to reduce the likelihood of the nebulizer solution reaching the eyes. Patients should be advised that ipratropium bromide inhalation solution can be mixed in the nebulizer with albuterol or metaproterenol if used within one hour. Drug stability and safety of ipratropium bromide inhalation solution when mixed with other drugs in a nebulizer have not been established. Patients should be reminded that ipratropium bromide inhalation solution should be used consistently as prescribed throughout the course of therapy.

Drug Interactions

Ipratropium bromide has been shown to be a safe and effective bronchodilator when used in conjunction with beta adrenergic bronchodilators. Ipratropium bromide has also been used with other pulmonary medications, including methylxanthines and corticosteroids, without adverse drug interactions.

Carcinogenesis, Mutagenesis, Impairment of Fertility

Two-year oral carcinogenicity studies in rats and mice have revealed no carcinogenic potential at dietary doses up to 6 mg/kg/day of ipratropium bromide.

Results of various mutagenicity studies (Ames test, mouse dominant lethal test, mouse micronucleus test and chromosome aberration of bone marrow in Chinese hamsters) were negative.

Fertility of male or female rats at oral doses up to 50 mg/kg/day was unaffected by ipratropium bromide inhalation solution administration. At doses above 90 mg/kg, increased resorption and decreased conception rates were observed.

Pregnancy

Teratogenic Effects

Pregnancy Category B

Oral reproduction studies performed in mice, rats and rabbits at doses of 10, 100 and 125 mg/kg respectively, and inhalation reproduction studies in rats and rabbits at doses of 1.5 and 1.8 mg/kg (or approximately 38 and 45 times the recommended human daily dose) respectively, have demonstrated no evidence of teratogenic effects as a result of ipratropium bromide inhalation solution. However, no adequate or well-controlled studies have been conducted in pregnant women. Because animal reproduction studies are not always predictive of human response, ipratropium bromide inhalation solution should be used during pregnancy only if clearly needed.

Nursing Mothers

It is not known whether ipratropium bromide is excreted in human milk. Although lipid-insoluble quaternary bases pass into breast milk, it is unlikely that ipratropium bromide would reach the infant to a significant extent, especially when taken by inhalation since ipratropium bromide inhalation solution is not well absorbed systemically after inhalation or oral administration. However, because many drugs are excreted in human milk, caution should be exercised when ipratropium bromide inhalation solution is administered to a nursing woman.

Pediatric Use

Safety and effectiveness in the pediatric population below the age of 12 have not been established.

ADVERSE REACTIONS

Adverse reaction information concerning ipratropium bromide inhalation solution is derived from 12-week active-controlled clinical trials. Additional information is derived from foreign post-marketing experience and the published literature.

All adverse events, regardless of drug relationship, reported by three percent or more patients in the 12-week controlled clinical trials appear in the table below.

Additional adverse reactions reported in less than three percent of the patients treated with ipratropium bromide include tachycardia, palpitations, eye pain, urinary retention, urinary tract infection and urticaria. Cases of precipitation or worsening of narrow-angle glaucoma and acute eye pain have been reported.

Lower respiratory adverse reactions (bronchitis, dyspnea and bronchospasm) were the most common events leading to discontinuation of ipratropium bromide therapy in the 12-week trials. Headache, mouth dryness and aggravation of COPD symptoms are more common when the total daily dose of ipratropium bromide equals or exceeds 2,000 mcg.

Allergic-type reactions such as skin rash, angioedema of tongue, lips and face, urticaria, laryngospasm and anaphylactic reaction have been reported. Many of the patients had a history of allergies to other drugs and/or foods.

All Adverse Events, from a Double-blind, Parallel, 12-week Study of Patients with COPD*

PERCENT OF PATIENTS
 | Ipratropium Bromide (500 mcg t.i.d) n=219 | Metaproterenol (15 mg t.i.d) n=212 | Ipratropium Bromide/ Metaproterenol (500 mcg t.i.d/15 mg t.i.d) n=108 | Albuterol (2.5 mg t.i.d) n=205 | Ipratropium Bromide/ Albuterol (500 mcg t.i.d/ 2.5 mg t.i.d) n=100
Body as a Whole-General Disorders
Headache | 6.4 | 5.2 | 6.5 | 6.3 | 9.0
Pain | 4.1 | 3.3 | 0.9 | 2.9 | 5.0
Influenza-like symptoms | 3.7 | 4.7 | 6.5 | 0.5 | 1.0
Back Pain | 3.2 | 1.9 | 1.9 | 2.4 | 0.0
Chest Pain | 3.2 | 4.2 | 5.6 | 2.0 | 1.0
Cardiovascular Disorders
Hypertension/ hypertension Aggravated | 0.9 | 1.9 | 0.9 | 1.5 | 4.0
Central & Peripheral Nervous System
Dizziness | 2.3 | 3.3 | 1.9 | 3.9 | 4.0
Insomnia | 0.9 | 0.5 | 4.6 | 1.0 | 1.0
Tremor | 0.9 | 7.1 | 8.3 | 1.0 | 0.0
Nervousness | 0.5 | 4.7 | 6.5 | 1.0 | 1.0
Gastrointestinal System Disorders
Mouth Dryness | 3.2 | 0.0 | 1.9 | 2.0 | 3.0
Nausea | 4.1 | 3.8 | 1.9 | 2.9 | 2.0
Constipation | 0.9 | 0.0 | 3.7 | 1.0 | 1.0
Musculo-skeletal System Disorders
Arthritis | 0.9 | 1.4 | 0.9 | 0.5 | 3.0
Respiratory System Disorders (Lower)
Coughing | 4.6 | 8.0 | 6.5 | 5.4 | 6.0
Dyspnea | 9.6 | 13.2 | 16.7 | 12.7 | 9.0
Bronchitis | 14.6 | 24.5 | 15.7 | 16.6 | 20.0
Bronchospasm | 2.3 | 2.8 | 4.6 | 5.4 | 5.0
Sputum Increased | 1.4 | 1.4 | 4.6 | 3.4 | 0.0
Respiratory Disorder | 0.0 | 6.1 | 6.5 | 2.0 | 4.0
Respiratory System Disorders (Upper)
Upper Respiratory Tract Infection | 13.2 | 11.3 | 9.3 | 12.2 | 16.0
Pharyngitis | 3.7 | 4.2 | 5.6 | 2.9 | 4.0
Rhinitis | 2.3 | 4.2 | 1.9 | 2.4 | 0.0
Sinusitis | 2.3 | 2.8 | 0.9 | 5.4 | 4.0

*All adverse events, regardless of drug relationship, reported by three percent or more patients in the 12-week controlled clinical trial.

OVERDOSAGE

Acute systemic overdosage by inhalation is unlikely since ipratropium bromide is not well absorbed after inhalation at up to four-fold the recommended dose, or after oral administration at up to forty-fold the recommended dose. The oral LD50of ipratropium bromide ranged between 1001 and 2010 mg/kg in mice; between 1667 and 4000 mg/kg in rats; and between 400 and 1300 mg/kg in dogs.

DOSAGE AND ADMINISTRATION

The usual dosage of ipratropium bromide inhalation solution is 500 mcg (1 Unit-Dose Vial) administered three to four times a day by oral nebulization, with doses 6 to 8 hours apart. Ipratropium bromide inhalation solution Unit-Dose Vials contain 500 mcg ipratropium bromide anhydrous in 2.5 mL normal saline. Ipratropium bromide inhalation solution can be mixed in the nebulizer with albuterol or metaproterenol if used within one hour. Drug stability and safety of ipratropium bromide inhalation solution when mixed with other drugs in a nebulizer have not been established.

HOW SUPPLIED

Ipratropium bromide inhalation solution is a clear, colorless solution containing 2.5 mL, packaged in cartons as listed below:

NDC 62135-830-84, 6 foil pouches, each containing 5 vials, total 30 vials per carton

Each vial is made from a low density polyethylene (LDPE) resin.

Storage and Handling

Store between 15° C and 30° C (59° F and 86° F). Protect from light. Store in pouch until time of use.

Rx Only

Manufactured for:
Chartwell RX, LLC.
Congers, NY 10920

L71925

Revised: 01/2024

Patient Package Insert

PATIENT’S INSTRUCTIONS FOR USE

Read complete instructions carefully before using.

1. Remove vial from the foil pouch, twist open the top of one unit-dose vial and squeeze the contents into the nebulizer reservoir (Figure 1).

2. Connect the nebulizer reservoir to the mouthpiece or face mask (Figure 2).

3. Connect the nebulizer to the compressor.
4. Sit in a comfortable, upright position; place the mouthpiece in your mouth (Figure 3) or put on the face mask and turn on the compressor. If a face mask is used, care should be taken to avoid leakage around the mask as temporary blurring of vision, pupil enlargement, precipitation or worsening of narrow angle glaucoma, or eye pain may occur if the solution comes into direct contact with the eyes.

5. Breathe as calmly, deeply and evenlyas possible until no more mist is formed in the nebulizer chamber (about 5 to 15 minutes). At this point, the treatment is finished.
6. Clean the nebulizer (see manufacturer’s instructions).

Note: Use only as directed by your physician. More frequent administration or higher doses are not recommended. Ipratropium bromide inhalation solution can be mixed in the nebulizer with albuterol or metaproterenol if used within one hour but not with other drugs. Drug stability and safety of ipratropium bromide inhalation solution when mixed with other drugs in a nebulizer have not been established.

Store between 15° C and 30° C (59° F and 86° F). Protect from light. Store in pouch until time of use.

L71925

Revised: 01/2024

PACKAGE LABEL.PRINCIPAL DISPLAY PANEL

Ipratropium Bromide Inhalation Solution, 0.02%, 2.5 mL - NDC 62135-830-84 - 2.5 mL Carton Label